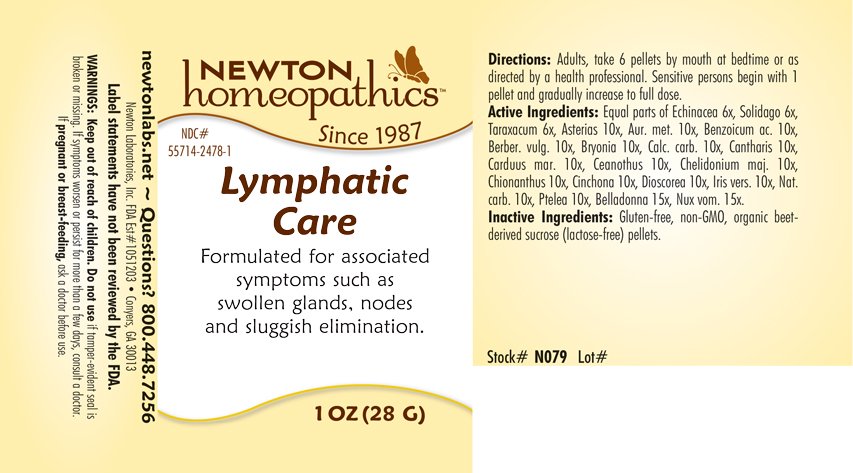 DRUG LABEL: Lymphatic Care
NDC: 55714-2478 | Form: PELLET
Manufacturer: Newton Laboratories, Inc.
Category: homeopathic | Type: HUMAN OTC DRUG LABEL
Date: 20250207

ACTIVE INGREDIENTS: BERBERIS VULGARIS ROOT BARK 10 [hp_X]/1 g; LYTTA VESICATORIA 10 [hp_X]/1 g; OYSTER SHELL CALCIUM CARBONATE, CRUDE 10 [hp_X]/1 g; ATROPA BELLADONNA 15 [hp_X]/1 g; BRYONIA ALBA ROOT 10 [hp_X]/1 g; ASTERIAS RUBENS 10 [hp_X]/1 g; CHIONANTHUS VIRGINICUS BARK 10 [hp_X]/1 g; CINCHONA OFFICINALIS BARK 10 [hp_X]/1 g; DIOSCOREA VILLOSA TUBER 10 [hp_X]/1 g; IRIS VERSICOLOR ROOT 10 [hp_X]/1 g; SODIUM CARBONATE 10 [hp_X]/1 g; STRYCHNOS NUX-VOMICA SEED 15 [hp_X]/1 g; PTELEA TRIFOLIATA BARK 10 [hp_X]/1 g; ECHINACEA, UNSPECIFIED 6 [hp_X]/1 g; TARAXACUM OFFICINALE 6 [hp_X]/1 g; SOLIDAGO VIRGAUREA FLOWERING TOP 6 [hp_X]/1 g; GOLD 10 [hp_X]/1 g; BENZOIC ACID 10 [hp_X]/1 g; MILK THISTLE 10 [hp_X]/1 g; CEANOTHUS AMERICANUS LEAF 10 [hp_X]/1 g; CHELIDONIUM MAJUS 10 [hp_X]/1 g
INACTIVE INGREDIENTS: SUCROSE

Lymphatic 2478P

INDICATIONS & USAGE SECTION

Formulated for associated symptoms such as swollen gland, nodes and sluggish elimination.

DOSAGE & ADMINISTRATION SECTION

Directions: Adults, take 6 pellets by mouth at bedtime or as directed by a health professional. Sensitive persons begin with 1 pellet and gradually increase to full dose.

OTC - ACTIVE INGREDIENT SECTION

Equal parts of Echinacea 6x, Solidago virgaurea 6x, Taraxacum officinale 6x, Asterias rubens 10x, Aurum metallicum 10x, Benzoicum acidum 10x, Berberis vulgaris 10x, Bryonia 10x, Calcarea carbonica 10x, Cantharis 10x, Carduus marianus 10x, Ceanothus americanus 10x, Chelidonium majus 10x, Chionanthus virginica 10x, Cinchona officinalis 10x, Dioscorea villosa 10x, Iris versicolor 10x, Natrum carbonicum 10x, Ptelea trifoliata 10x, Belladonna 15x, Nux vomica 15x.

OTC - PURPOSE SECTION

Formulated for associated symptoms such as swollen glands, nodes and sluggish elimination.

INACTIVE INGREDIENT SECTION

I nactive Ingredients: Gluten-free, non-GMO, organic beet-derived sucrose (lactose-free) pellets.

QUESTIONS SECTION

newtonlabs.net - Questions? 800.448.7256

Newton Laboratories, Inc. FDA Est # 1051203 Conyers, GA 30013

WARNINGS SECTION

WARNINGS: Keep out of reach of children. Do not use if tamper-evident seal is broken or missing. If symptoms worsen or persist for more than a few days, consult a doctor. If pregnant or breast-feeding, ask a doctor before use.

OTC - PREGNANCY OR BREAST FEEDING SECTION

If pregnant or breast-feeding, ask a doctor before use.

OTC - KEEP OUT OF REACH OF CHILDREN

Keep out of reach of children.